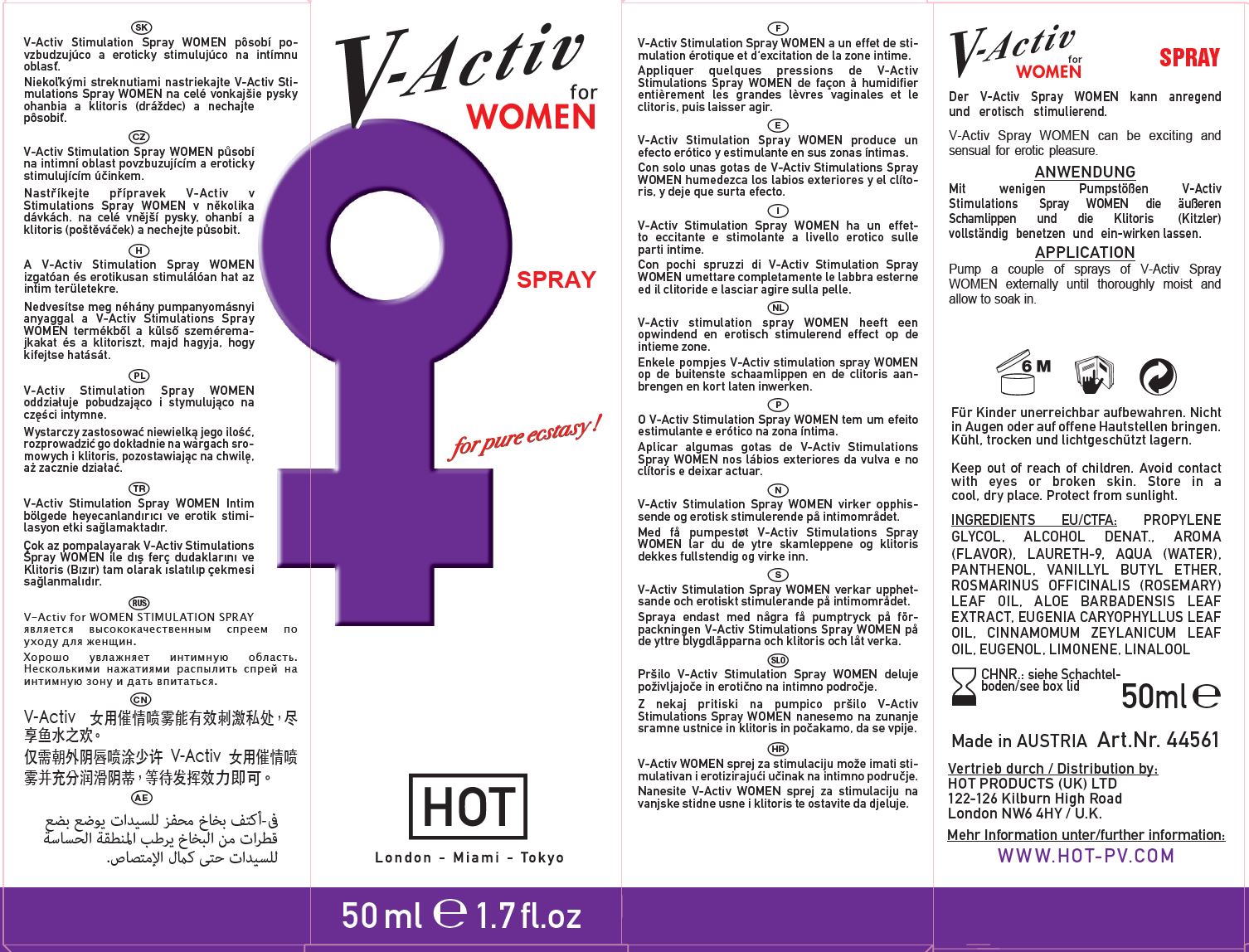 DRUG LABEL: V-ACTIV FOR WOMEN
NDC: 71326-205 | Form: SPRAY
Manufacturer: HOT PRODUCTIONS AND VERTRIEBS GMBH
Category: homeopathic | Type: HUMAN OTC DRUG LABEL
Date: 20231005

ACTIVE INGREDIENTS: CINNAMON LEAF OIL 0.1 g/100 mL
INACTIVE INGREDIENTS: EUGENOL; ROSEMARY OIL; WATER; POLIDOCANOL; VANILLYL BUTYL ETHER; PANTHENOL; CLOVE LEAF OIL; LIMONENE, (+)-; LINALOOL, (+)-; PROPYLENE GLYCOL; ALCOHOL

HOT PRODUCTS - V-ACTIV FOR WOMEN SPRAY (71326-205)

ACTIVE INGREDIENTS

CINNAMOMUM ZEYLANICUM LEAF OIL 0.1X HPUS

PURPOSE

Topical stimulation

USE

V-Activ Spray WOMEN can be exciting and sensual for erotic pleasure.

WARNINGS

Avoid contact with the eyes or broken skin.

Keep out of reach of children. If product is accidentally swallowed, get medical help or contact a Poison Control Center right away.

DIRECTIONS

Pump a couple of sprays of V-Activ Spray WOMEN externally until thoroughly moist and allow to soak in.

OTHER INFORMATION

- Store in a cool, dry place. Protect from sunlight.

INACTIVE INGREDIENTS

PROPYLENE GLYCOL, ALCOHOL DENAT., AROMA (FLAVOR), LAURETH-9, AQUA (WATER), PANTHENOL, VANILLYL BUTYL ETHER, ROSMARINUS OFFICINALIS (ROSEMARY) LEAF OIL, ALOE BARBADENSIS LEAF EXTRACT, EUGENIA CARYOPHYLLUS LEAF OIL, CINNAMOMUM ZEYLANICUM LEAF OIL, EUGENOL, LIMONENE, LINALOOL